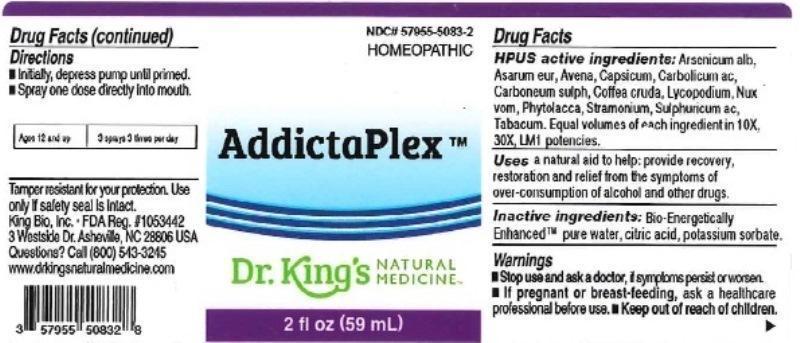 DRUG LABEL: AddictaPlex
NDC: 57955-5083 | Form: LIQUID
Manufacturer: King Bio Inc.
Category: homeopathic | Type: HUMAN OTC DRUG LABEL
Date: 20160321

ACTIVE INGREDIENTS: ARSENIC TRIOXIDE 10 [hp_X]/59 mL; ASARUM EUROPAEUM 10 [hp_X]/59 mL; AVENA SATIVA FLOWERING TOP 10 [hp_X]/59 mL; CAPSICUM 10 [hp_X]/59 mL; PHENOL 10 [hp_X]/59 mL; CARBON DISULFIDE 10 [hp_X]/59 mL; ARABICA COFFEE BEAN 10 [hp_X]/59 mL; LYCOPODIUM CLAVATUM SPORE 10 [hp_X]/59 mL; STRYCHNOS NUX-VOMICA SEED 10 [hp_X]/59 mL; PHYTOLACCA AMERICANA ROOT 10 [hp_X]/59 mL; DATURA STRAMONIUM 10 [hp_X]/59 mL; SULFURIC ACID 10 [hp_X]/59 mL; TOBACCO LEAF 10 [hp_X]/59 mL
INACTIVE INGREDIENTS: WATER; ANHYDROUS CITRIC ACID; POTASSIUM SORBATE

AddictaPlex™

ACTIVE INGREDIENT

Drug Facts__________________________________________________________________________________________________________

HPUS active ingredients: Arsenicum album, Asarum europaeum, Avena sativa, Capsicum annuum, Carbolicum acidum, Carboneum sulphuratum, Coffea cruda, Lycopodium clavatum, Nux vomica, Phytolacca decandra, Stramonium, Sulphuricum acidum, Tabacum. Equal volumes of each ingredient in 10X, 30X, and LM1 potencies.

INDICATIONS AND USAGE

Uses a natural aid to help: provide recovery, restoration and relief from the symptoms of over-consumption of alcohol and other drugs.

Inactive Ingredients:

Bio-Energetically Enhanced™ pure water, citric acid and potassium sorbate.

Warnings

- Stop use and ask your doctor if symptoms persist or worsen.
- If pregnant or breast-feeding, ask a healthcare professional before ues.

- Keep out of reach of children.

Directions

- Initially, depress pump until primed.
- Spray one dose directly into mouth.
- Ages 12 and up: 3 sprays 3 times per day.

OTHER SAFETY INFORMATION

Tamper resistant for your protection. Use only if safety seal is intact.

PURPOSE

Uses a natural aid to help:

- provide recovery
- restoration and relief from the symptoms of over-consumption of alcohol and other drugs.